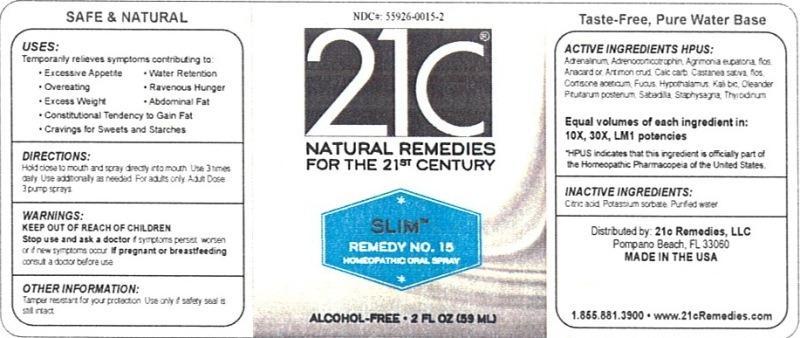 DRUG LABEL: Slim Remedy No. 15
NDC: 55926-0015 | Form: LIQUID
Manufacturer: Speer Laboratories, LLC
Category: homeopathic | Type: HUMAN OTC DRUG LABEL
Date: 20130731

ACTIVE INGREDIENTS: EPINEPHRINE 10 [hp_X]/59 mL; CORTICOTROPIN 10 [hp_X]/59 mL; AGRIMONIA EUPATORIA FLOWER 10 [hp_X]/59 mL; SEMECARPUS ANACARDIUM JUICE 10 [hp_X]/59 mL; ANTIMONY TRISULFIDE 10 [hp_X]/59 mL; OYSTER SHELL CALCIUM CARBONATE, CRUDE 10 [hp_X]/59 mL; CASTANEA SATIVA FLOWER 10 [hp_X]/59 mL; CORTISONE ACETATE 10 [hp_X]/59 mL; FUCUS VESICULOSUS 10 [hp_X]/59 mL; BOS TAURUS HYPOTHALAMUS 10 [hp_X]/59 mL; POTASSIUM DICHROMATE 10 [hp_X]/59 mL; NERIUM OLEANDER LEAF 10 [hp_X]/59 mL; SUS SCROFA PITUITARY GLAND 10 [hp_X]/59 mL; SCHOENOCAULON OFFICINALE SEED 10 [hp_X]/59 mL; DELPHINIUM STAPHISAGRIA SEED 10 [hp_X]/59 mL; THYROID, UNSPECIFIED 10 [hp_X]/59 mL
INACTIVE INGREDIENTS: CITRIC ACID MONOHYDRATE; POTASSIUM SORBATE; WATER

Slim Remedy No. 15

Active Ingredient HPUS: Adrenalinum, Adrenocorticotrophin, Agrimonia eupatoria, flos, Anacardium orientale, Antimonium crudum, Calcarea carbonica, Castanea sativa, flos, Cortisone aceticum, Fucus vesiculosus, Hypothalamus, Kali bichromicum, Oleander, Pituitarum posterium, Sabadilla, Staphysagria, Thyroidinum.

Equal volumes of each ingredient in: 10X, 30X, LM1 potencies.

HPUS indicates that this ingredient is officially part of the Homeopathic Pharmacopia of the United States.

Inactive Ingredients: Citric acid, Potassium sorbate, Purified water.

INDICATIONS AND USAGE

Uses: Temporarily relieves symptoms contributing to:

- excessive appetite
- overeating
- excess weight
- consitutional tendency to gain fat
- cravings for sweets and starches
- water retention
- ravenous hunger
- abdominal fat

DOSAGE AND ADMINISTRATION

Directions: Hold close to mouth and spray directly into mouth. Use 3 times daily. Use additionally as needed. For adults only. Adult Dose: 3 pump sprays.

Keep out of reach of children.

Warnings:

Stop use and ask a doctor if symptoms persist, worsen or if new symptoms occur. If pregnant or breastfeeding, consult a doctor before use.

Other Information: Tamper resistant for your protection. Use only if safety seal is still intact.

PURPOSE

Uses: Temporarily relieves symptoms contributing to: excessive appetite, overeating, excess weight, consitutional tendency to gain fat, cravings for sweets and starches, water retention, ravenous hunger and abdominal fat.